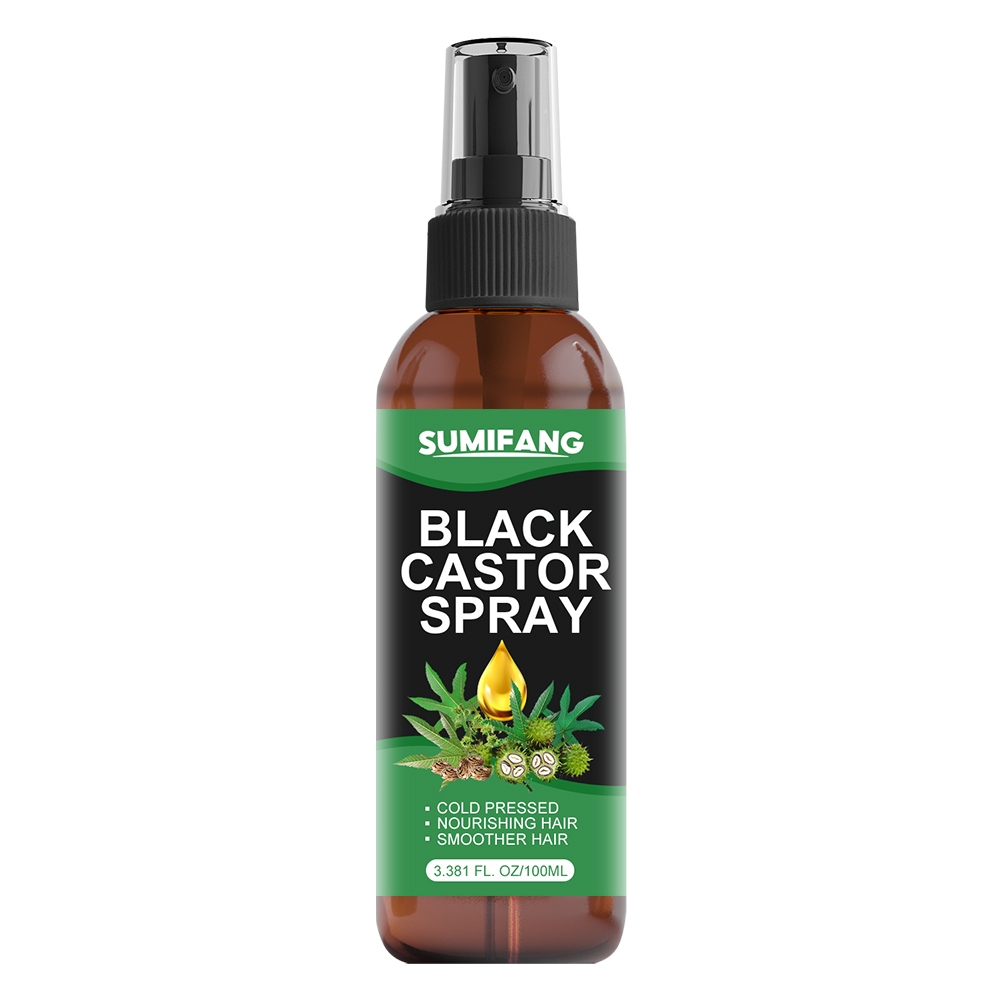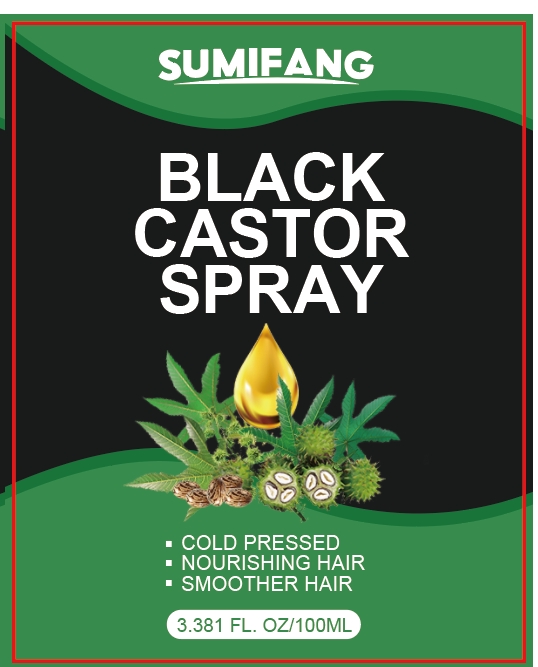 DRUG LABEL: BLACK CASTORSPRAY
NDC: 84025-154 | Form: SPRAY
Manufacturer: Guangzhou Yanxi Biotechnology Co.. Ltd
Category: otc | Type: HUMAN OTC DRUG LABEL
Date: 20240817

ACTIVE INGREDIENTS: ASCORBIC ACID 5 mg/100 mL; PANTHENOL 3 mg/100 mL
INACTIVE INGREDIENTS: WATER

DOSAGE AND ADMINISTRATION

Spray for moisturizing and smoothing hair

WARNINGS

Keep out of children

INACTIVE INGREDIENT

Aqua

INDICATIONS AND USAGE

For daily hair and scalp care

Keep out of children

PURPOSE

Effectively moisturizes the hair and keeps the hair smooth and non-sticky